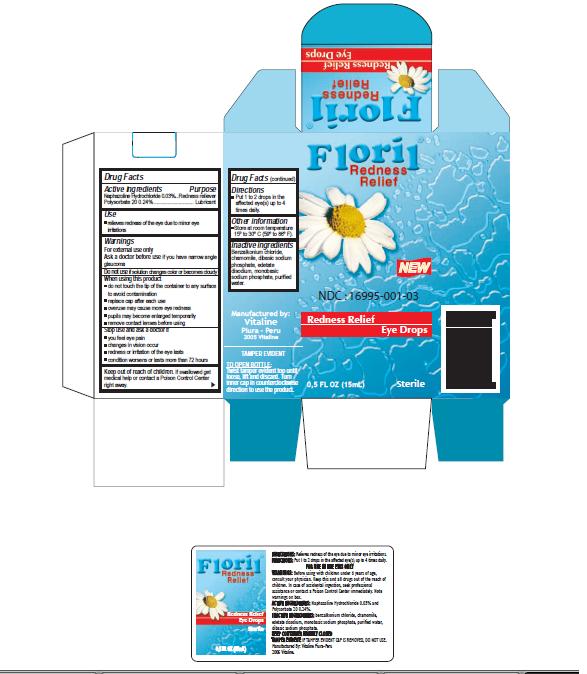 DRUG LABEL: FLORIL REDNESS RELIEF
NDC: 16995-001 | Form: SOLUTION/ DROPS
Manufacturer: VITALINE S.A.C.
Category: otc | Type: HUMAN OTC DRUG LABEL
Date: 20100107

ACTIVE INGREDIENTS: NAPHAZOLINE HYDROCHLORIDE 3 mg/10 mL; POLYSORBATE 20 2 mg/1 mL
INACTIVE INGREDIENTS: LIME 353 mg/10000 mL

Actives ingredients Purpose

Naphazoline Hydrocloride 0,03% redness reliever
Polysorbate 20 0,24% Lubricant

Inactive ingredients

Benzalkonium chloride, chamomile, dibasic sodium phosphate, edetate disodium, monobasic sodium phosphate, purified water.

WARNINGS

For external use only

Ask a doctor before use if you have narrow angle glaucoma

Do not use if the solution changes color or becomes cloudy

WHEN USING

- do not touch the tip of the container to any surface to avoid contamination
- replace cap after each use
- overuse may cause more eye redness
- pupils may become enlarged temporarily
- remove contact lenses before using

Stop use and ask doctor if

- you feel eye pain
- changes in vision occur
- redness or irritation of the eye lasts
- condition worsens or lasts more than 72 hours

KEEP OUT OF REACH OF CHILDREN

If swallowed get medical help or contact a Poison Control Center right away

Use

Relieves redness of the eye due to minor eye irritations

Directions

Put 1 to 2 drops in the affected eye(s) up to 4 times daily.

Other information

Store at room temperature 15° to 30° (59° to 86° F).